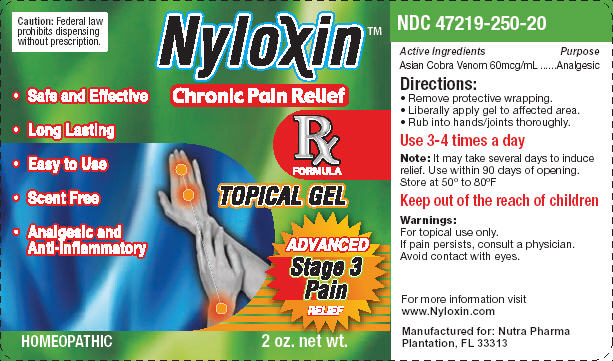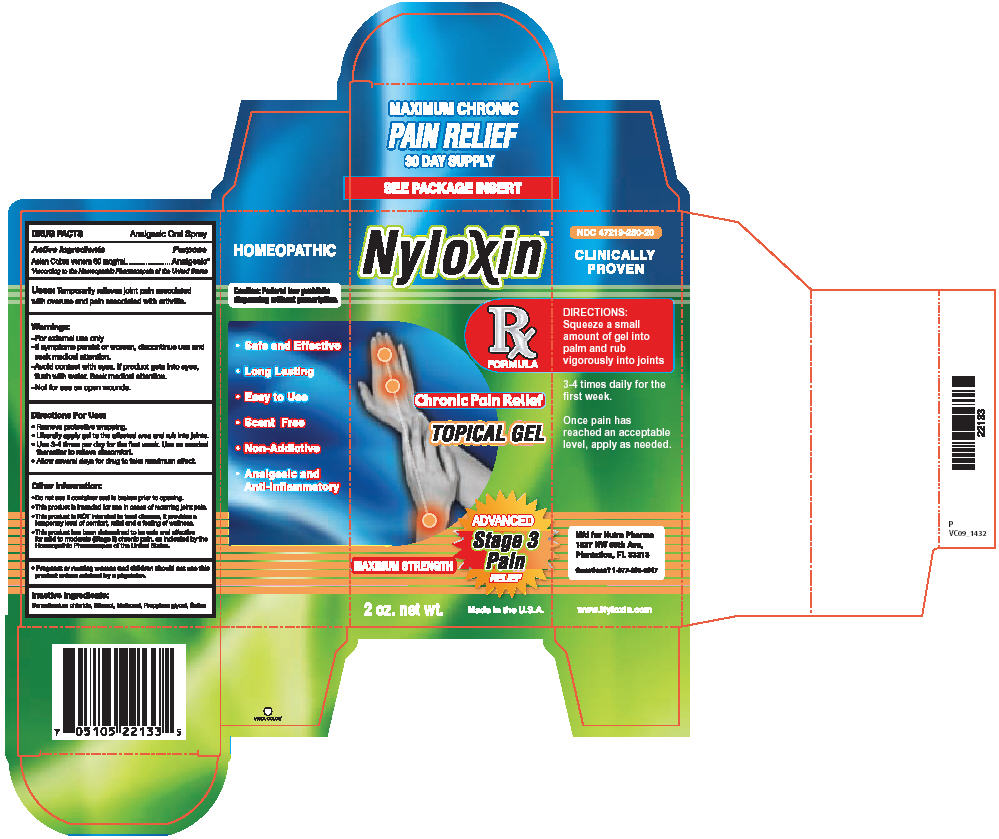 DRUG LABEL: NYLOXIN
NDC: 47219-253 | Form: GEL
Manufacturer: RECEPTOPHARM INC
Category: homeopathic | Type: HUMAN OTC DRUG LABEL
Date: 20091130

ACTIVE INGREDIENTS: NAJA NAJA VENOM 60 ug/1 mL
INACTIVE INGREDIENTS: DIPROPYLENE GLYCOL; BENZALKONIUM CHLORIDE; 2-(DIETHYLAMINO)ETHANOL; SODIUM CHLORIDE; HYDROXYPROPYL CELLULOSE

DRUG FACTS

Active Ingredients

Asian Cobra venom 60 mcg/mL

Purpose

Analgesic [According to the Homeopathic Pharmacopeia of the United States]

INDICATIONS AND USAGE

Uses: Temporarily relieves joint pain associated with overuse and pain associated with arthritis.

Warnings:

- For external use only
- If symptoms persist or worsen, discontinue use and seek medical attention.
- Avoid contact with eyes. If product gets into eyes, flush with water. Seek Medical attention.
- Not for use on open wounds.

Directions For Use:

- Remove protective wrapping.
- Liberally apply gel to the affected area and rub into joints.
- Use 3-4 times per day for the first week. Use as needed thereafter to relieve discomfort.
- Allow several days for drug to take maximum effect.

Other Information:

- Do not use if container seal is broken prior to opening.
- This product is intended for use in cases of recurring joint pain.
- This product is NOT intended to treat disease. It provides a temporary level of comfort, relief, and a feeling of wellness.
- This product has been determined to be safe and effective for mild to moderate (Stage 2) chronic pain, as indicated by the Homeopathic Pharmacopeia of the United States.

- Pregnant or nursing women and children should not use this product unless advised by a physician.

Inactive Ingredients:

Benzalkonium chloride, Ethanol, Methocel, Propylene glycol, Saline

PACKAGE LABEL

Package Label - Principal Display Panel – 2.0 oz Gel Label

PACKAGE LABEL

Package Label - Principal Display Panel – 2.0 oz Gel Carton